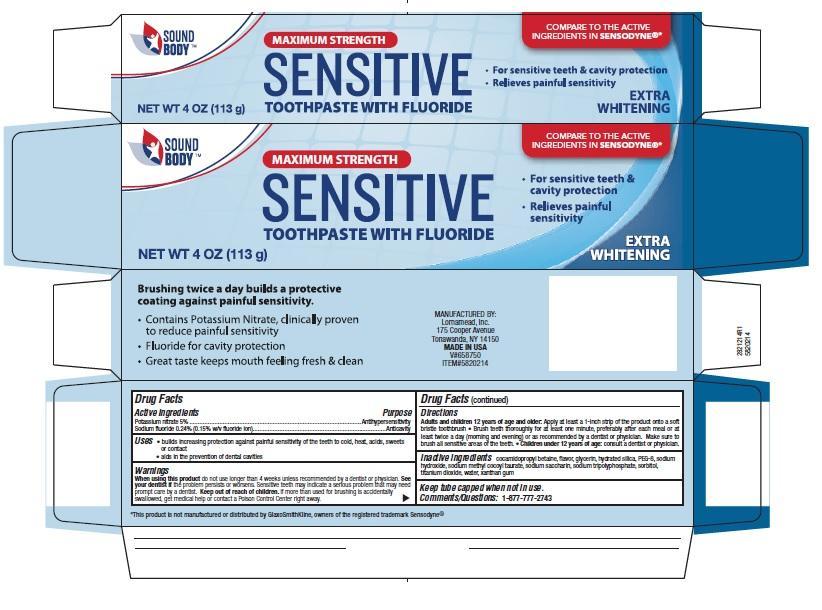 DRUG LABEL: Sound Body Sensitive
NDC: 50594-214 | Form: PASTE, DENTIFRICE
Manufacturer: Big Lots Stores, Inc.
Category: otc | Type: HUMAN OTC DRUG LABEL
Date: 20251114

ACTIVE INGREDIENTS: SODIUM FLUORIDE 0.15 g/100 g; POTASSIUM NITRATE 5 g/100 g
INACTIVE INGREDIENTS: WATER; SACCHARIN SODIUM; SODIUM TRIPOLYPHOSPHATE; POLYETHYLENE GLYCOL 400; SORBITOL; TITANIUM DIOXIDE; SODIUM HYDROXIDE; GLYCERIN; XANTHAN GUM; HYDRATED SILICA; COCAMIDOPROPYL BETAINE; SODIUM METHYL COCOYL TAURATE

5820214 Sound Body Max Str Sensitive Toothpaste with Fluoride (8015201)

Drug Facts

Active ingredients

Potassium nitrate 5%

Sodium fluoride 0.24% (0.15% w/v fluoride ion)

Purpose

Antihypersensitivity

Anticavity

Uses

- builds increasing protection against painful sensitivity of the teeth to cold, heat, acids, sweets or contact
- aids in the prevention of dental cavities

Warnings

WHEN USING

When using this productdo not use longer than 4 weeks unless recommended by a dentist or physician.

STOP USE

See your dentistif the problem worsens. Sensitive teeth may indicate a serious problem that may need prompt care by a dentist.

Keep out of reach of children. If more than used for brushing is accidentally swallowed, get medical help or contact a Poison Control Center right away.

Directions

Adults and children 12 years of age and older:Apply at least a 1-inch strip of the product onto a soft bristle toothbrush.

- Brush teeth thoroughly for at least one minute, preferably after each meal or at least twice a day (morning and evening) or as recommended by a dentist or physican. Make sure to brush all sensitive areas of the teeth.
- Children under 12 years of age:consult a dentist or physician.

INACTIVE INGREDIENT

Inactive ingredientscocamidopropyl betaine, flavor, glycerin, hydrated silica, PEG-8, sodium hydroxide, sodium methyl cocoyl taurate, sodium saccharin, sodium tripolyphosphate, sorbitol, titanium dioxide, water, xanthan gum

Comments/Questions:1-877-777-2743

MANUFACTURED BY:

Lornamead, Inc.

175 Cooper Avenue

Tonawanda, NY 14150

MADE IN USA

PACKAGE LABEL

SOUND BODY

MAXIMUM STRENGTH

SENSITIVE TOOTHPASTE WITH FLUORIDE

- For sensitive teeth & cavity protection
- Relieves painful sensitivity

EXTRA WHITENING

NET WT 4 OZ (113 g)